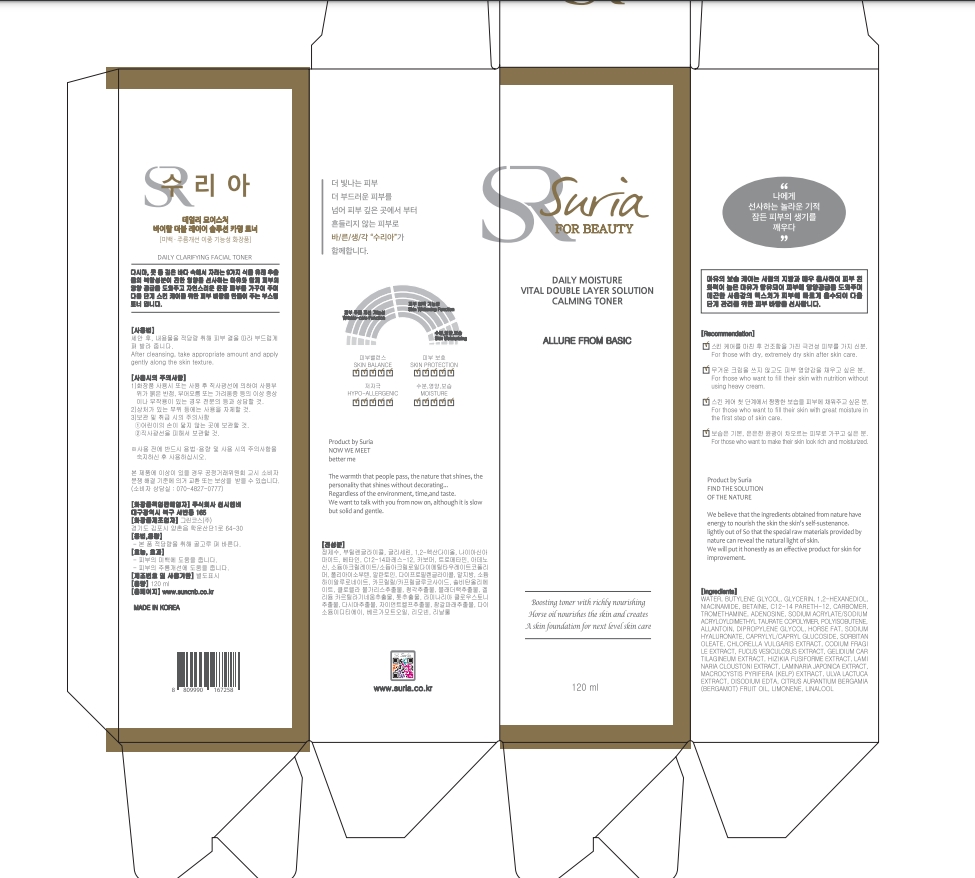 DRUG LABEL: SURIA CALMING TONER
NDC: 81479-003 | Form: LIQUID
Manufacturer: SUN C&B
Category: otc | Type: HUMAN OTC DRUG LABEL
Date: 20210207

ACTIVE INGREDIENTS: GLYCERIN 3 g/120 mL; NIACINAMIDE 2 g/120 mL
INACTIVE INGREDIENTS: WATER 115 g/120 mL

ACTIVE INGREDIENT

NIACINAMIDE

INACTIVE INGREDIENT

WATER,ETC

PURPOSE

Purpose:This combination of cosmetics is used for your basic skin care and gives a benefit for Brightening care.

WARNINGS

Warnings:For external use only. Avoid contact with eyes. Discontinue use if signs of irritation appear.

Keep out of reach of children:Keep out of reach of children.

INDICATIONS AND USAGE

Indication and usage:Following emulsion, pour some on the palm of your hand and apply to skin gently. Press down lightly until absorbed.

Dosage and administration:Take appropriate amount according to your skin condition and apply every morning and night.